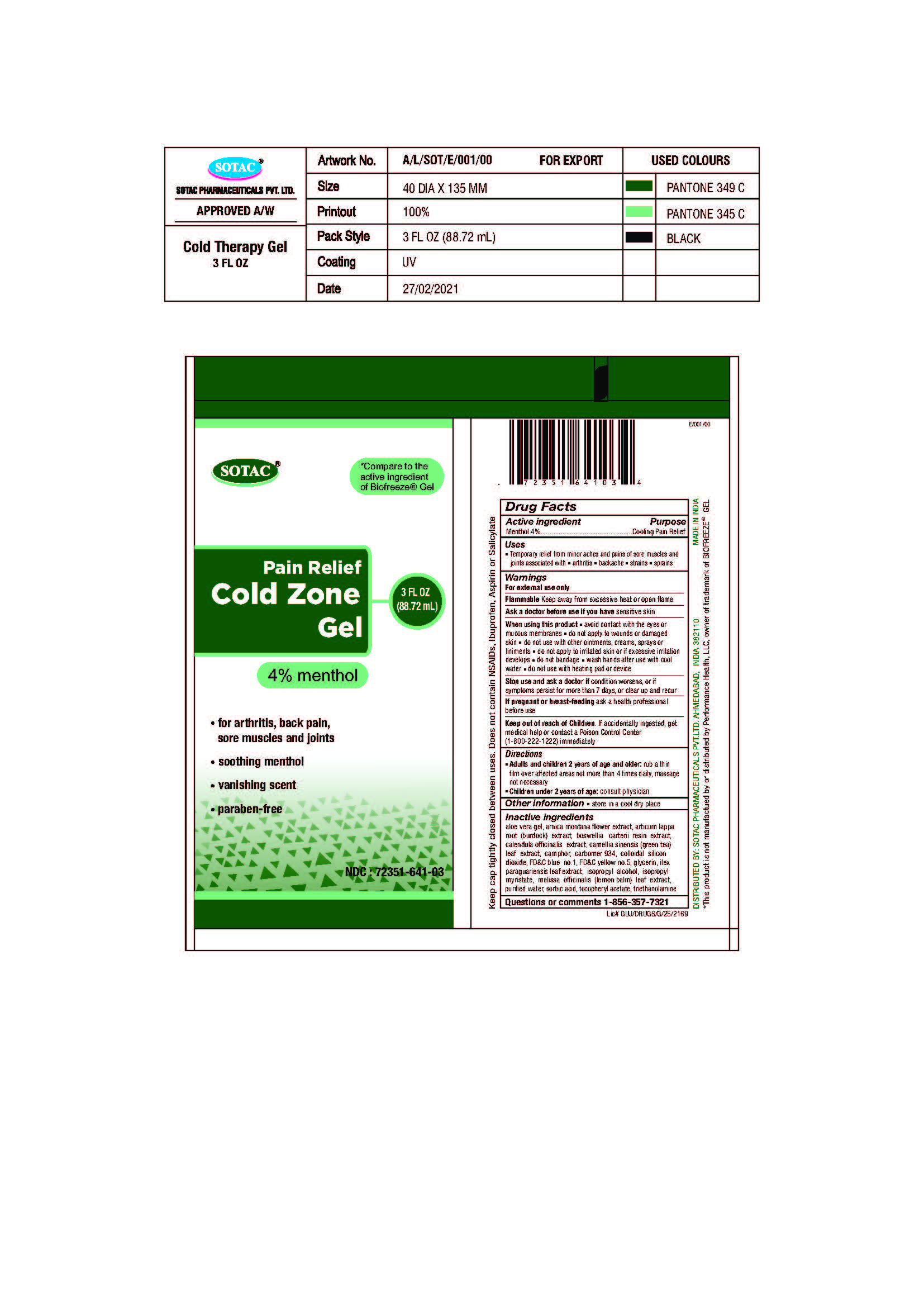 DRUG LABEL: Pain Relief Cold Therapy Gel 3 FL OZ
NDC: 72351-641 | Form: GEL
Manufacturer: SOTAC PHARMACEUTICAL PRIVATE LIMITED
Category: otc | Type: HUMAN OTC DRUG LABEL
Date: 20221231

ACTIVE INGREDIENTS: MENTHOL 40 mg/1 mL
INACTIVE INGREDIENTS: SILICON DIOXIDE; .ALPHA.-TOCOPHEROL ACETATE; WATER; ARCTIUM LAPPA ROOT; ISOPROPYL ALCOHOL; FD&C YELLOW NO. 5; CAMPHOR (NATURAL); CARBOMER 934; GLYCERIN; FRANKINCENSE; CALENDULA OFFICINALIS FLOWER; FD&C BLUE NO. 1; ILEX PARAGUARIENSIS LEAF; ISOPROPYL MYRISTATE; GREEN TEA LEAF; TROLAMINE; ARNICA MONTANA FLOWER; BRILLIANT BLUE G; MELISSA OFFICINALIS LEAF; ALOE VERA LEAF; SORBIC ACID

Active Ingredient

Menthol 4%

Purpose

Cooling Pain Relief

Uses

Temporary relief from minor aches and pains of sore muscles and
joints associated with •arthritis •backache •strains •sprains

Warnings

For external use only

Flammable

Keep away from excessive heat or open flame

Ask a doctor before use if you have

sensitive skin

When using this product

• avoid contact with the eyes or mucous membranes

• do not apply to wounds or damaged skin

• do not use with other ointments, creams, sprays or liniments

• do not apply to irritated skin or if excessive irritation develops

• do not bandage

• wash hands after use with cool water

• do not use with heating pad or device

Stop use and ask a doctor if

condition worsens, or if symptoms persist for more than 7 days, or clear up and recur

If pregnant or breast-feeding

ask a health professional before use

Keep out of reach of Children.

If accidentally ingested, get medical help or contact a Poison Control Center (1-800-222-1222) immediately

Directions

• Adults and children 2 years of age and older: rub a thin film over affected areas not more than 4 times daily, massage not necessary

• Children under 2 years of age: consult physician

Other Information

• store in a cool dry place

Inactive ingredients

aloe vera gel, arnica montana flower extract, articum lappa root (burdock) extract, boswellia carterii resin extract, calendula officinalis extract, camellia sinensis (green tea) leaf extract, camphor, carbomer 934, colloidal silicon dioxide, FD&C blue no.1, FD&C yellow no.5, glycerin, ilex paraguariensis leaf extract, isopropyl alcohol, isopropyl myristate, melissa officinalis (lemon balm) leaf extract, purified water, sorbic acid, tocopheryl acetate, triethanolamine

Questions or comments

1-856-357-7321